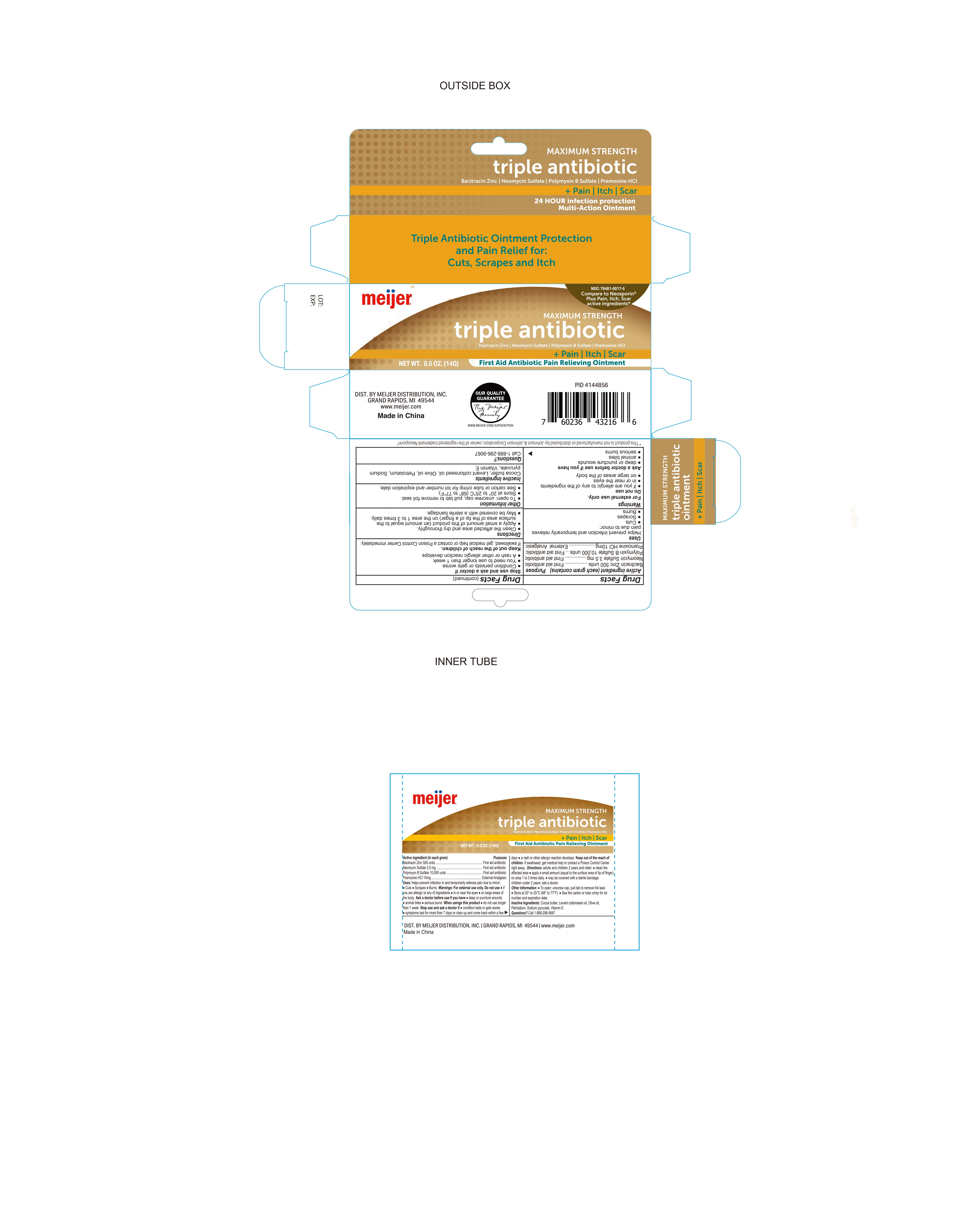 DRUG LABEL: Triple antibiotic and pain itch scar
NDC: 79481-0017 | Form: OINTMENT
Manufacturer: Meijer
Category: otc | Type: HUMAN OTC DRUG LABEL
Date: 20230111

ACTIVE INGREDIENTS: BACITRACIN ZINC 500 [USP'U]/1 g; NEOMYCIN SULFATE 3.5 mg/1 g; PRAMOXINE HYDROCHLORIDE 10 mg/1 g; POLYMYXIN B SULFATE 10000 [USP'U]/1 g
INACTIVE INGREDIENTS: COCOA BUTTER; SODIUM PYRUVATE; PETROLATUM; OLIVE OIL; LEVANT COTTONSEED OIL; .ALPHA.-TOCOPHEROL

Meijer Triple Antibiotic + Pain Itch Scar

Active Ingredient

Bacitracin zinc 500 Units

Purpose

First Aid Antibiotic

Active Ingredient

Neomycin Sulfate 3.5mg

Purpose

First Aid Antibiotic

Active Ingredient

Polymyxin B Sulfate 10,000 Units

Purpose

First Aid Antibiotic

Active Ingredient

Pramoxine HCL 10mg

Purpose

External Analgesic

Uses

Helps prevent infection and temporarily relieves pain due to minor:

- Cuts
- Scrapes
- Burns

Warnings

For external use only. Do not use:

- In or near the eyes
- On large areas of the body
- If you are allergic to any of the ingredients

Ask a Doctor before Use

Ask Doctor before use if you have:

- Deep or puncture wounds
- Animal bites
- Serious burns

Stop Use and ask a Doctor if:

- Condition persists or gets worse
- You need to use longer than 1 week
- A rash or other allergic reaction develops

When using this product

do not use longer than 1 week.

Keep out of Reach of Children

If Swallowed, get medical help or contact a Poison Control Center immediately.

Directions

- Adults and children 2 years and older:
- Clean the affected area and dry thoroughly
- Apply a small amount of this product (an amount equal to the surface area of the tip of a finger) on the area 1 to 3 times daily
- May be covered with a sterile bandage

Children under 2 years: ask a doctor

Other Information

- To Open: Unscrew cap, pull tab to remove foil seal
- Store at 20° to 25°C (68° to 77°F)
- See carton or tube crimp for lot number and expiration date

Inactive Ingredient:

Cocoa Butter, Levant Cottonseed Oil, Olive Oil, Petrolatum, Sodium Pyruvate, Vitamin E

Other Information

Distributed By:

Meijer Distribution Inc.

Grand Rapids, MI 49644

www.meijer.com

Made in China

This product is not manufactured or distributed by Johnson & Johnson Corporation, owner of registered trademark Neosporin

Questions?

Call 1-888-296-9067